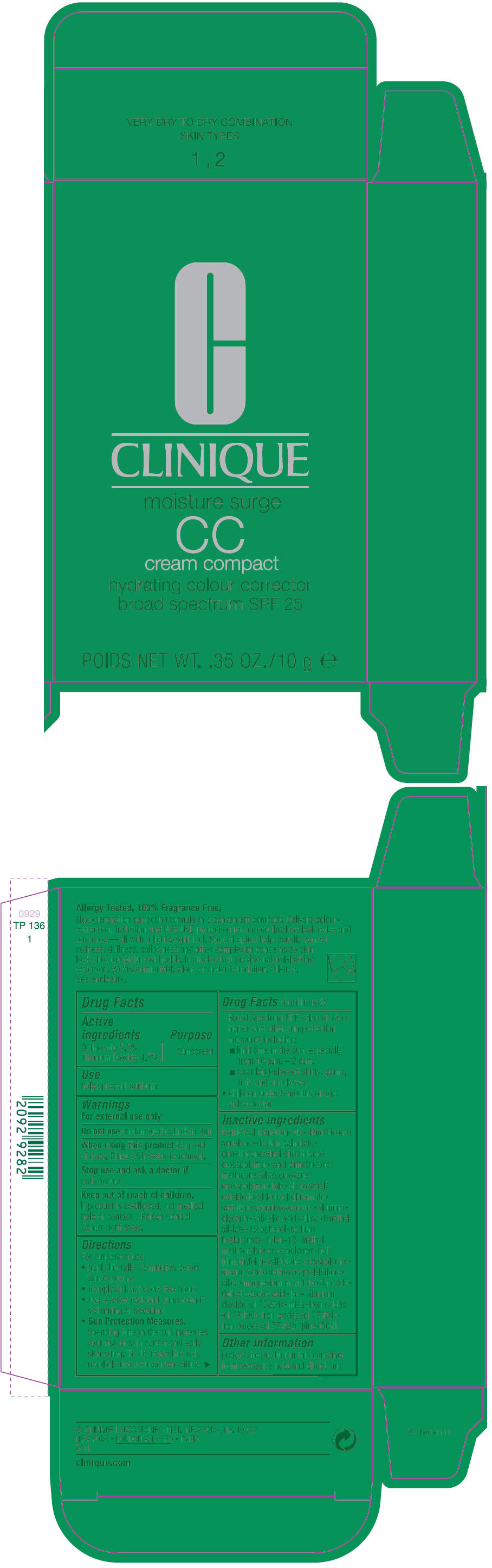 DRUG LABEL: CLINIQUE 
NDC: 49527-040 | Form: CREAM
Manufacturer: CLINIQUE  LABORATORIES INC.
Category: otc | Type: HUMAN OTC DRUG LABEL
Date: 20140106

ACTIVE INGREDIENTS: OCTINOXATE 5.5 g/100 g; TITANIUM DIOXIDE 4.7 g/100 g
INACTIVE INGREDIENTS: ISOTRIDECYL ISONONANOATE; DIMETHICONE; SQUALANE; TALC; ALUMINUM OXIDE; GLYCERIN; SALICYLIC ACID; SILICA DIMETHYL SILYLATE; TOCOPHEROL; HYALURONATE SODIUM; NYLON-12; STEARIC ACID; TRIETHOXYCAPRYLYLSILANE; SILICON DIOXIDE; MAGNESIUM MYRISTATE; STANNIC OXIDE; DEHYDROACETIC ACID; MICA; FERROSOFERRIC OXIDE; FERRIC OXIDE RED; FERRIC OXIDE YELLOW

MOISTURE SURGE CC COMPACT HYDRATING COLOUR CORRECTOR BROAD SPECTRUM SPF 25

Drug Facts

Active ingredients

Octinoxate 5.5%
Titanium Dioxide 4.7%

Purpose

Sunscreen

Use

helps prevent sunburn

Warnings

For external use only

Do not use on damaged or broken skin

When using this product keep out of eyes. Rinse with water to remove.

Stop use and ask a doctor if rash occurs

Keep out of reach of children.

If product is swallowed, get medical help or contact a Poison Control Center right away.

Directions

For sunscreen use:

- apply liberally 15 minutes before sun exposure
- reapply at least every two hours
- use a water resistant sunscreen if swimming or sweating
- Sun Protection Measures.
  Spending time in the sun increases your risk of skin cancer and early skin aging. To decrease this risk, regularly use a sunscreen with a Broad Spectrum SPF value of 15 or higher and other sun protection measures including:
  - limit time in the sun, especially from 10 a.m. – 2 p.m.
  - wear long-sleeved shirts, pants, hats and sunglasses
- children under 6 months of age:
  ask a doctor

Inactive ingredients

isotridecyl isononanoate • dimethicone • squalane • dextrin palmitate • dimethicone/vinyl dimethicone crosspolymer • vinyl dimethicone/methicone silsesquioxane crosspolymer • talc • phytosteryl/octyldodecyl lauroyl glutamate • sorbitan sesquiisostearate • alumina • glycerin • salicylic acid • silica dimethyl silylate • tocopherol • sodium hyaluronate • nylon-12 • methyl methacrylate crosspolymer • hdi/trimethylol hexyllactone crosspolymer • stearic acid • triethoxycaprylylsilane • silica • magnesium myristate • tin oxide • dehydroacetic acid • [+/- titanium dioxide (ci 77891) • mica • iron oxides (ci 77499) • iron oxides (ci 77491) • iron oxides (ci 77492)] [iln40504]

Other information

protect the product in this container from excessive heat and direct sun

PRINCIPAL DISPLAY PANEL - 10 g Tube Carton

C

CLINIQUE

moisture surge

cc
cream compact

hydrating colour corrector
broad spectrum SPF 25

POIDS NET WT. .35 OZ./10 g e